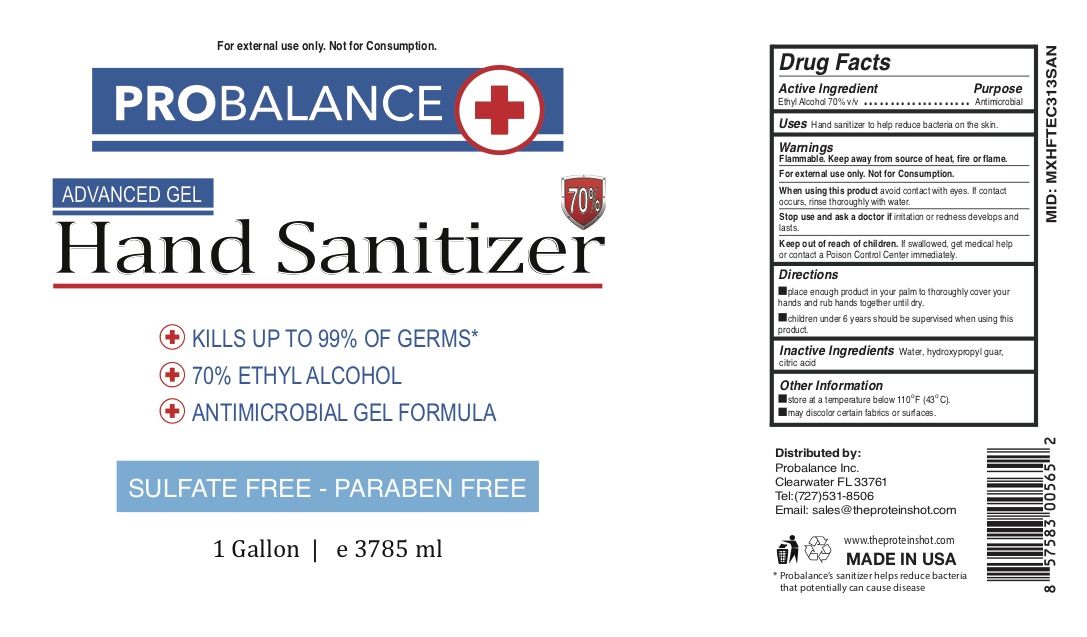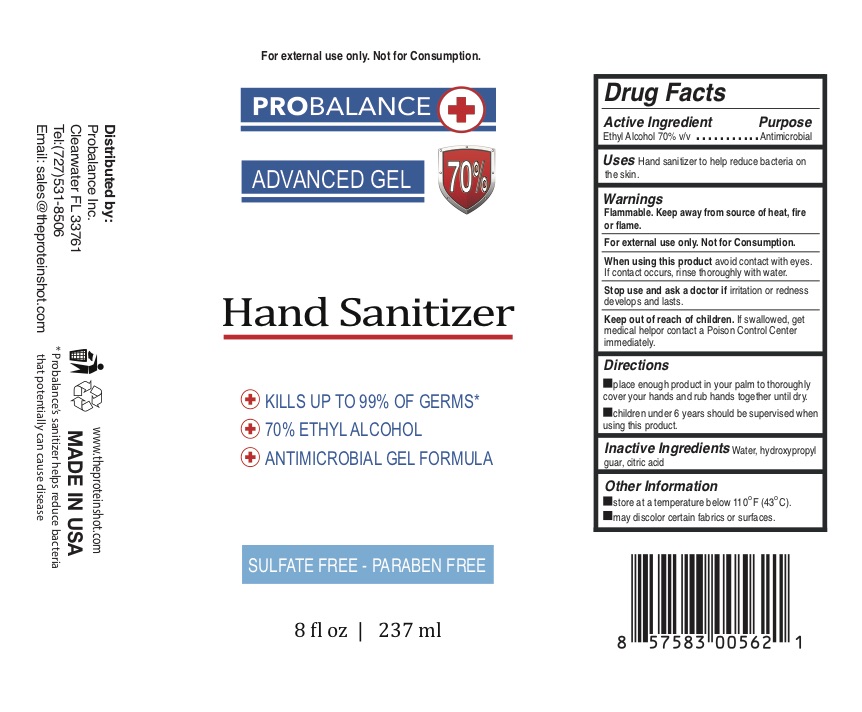 DRUG LABEL: PROBALANCE Hand Sanitizer Advanced
NDC: 78072-501 | Form: GEL
Manufacturer: LTD ENTERPRISES DISTRIBUTION, INC.
Category: otc | Type: HUMAN OTC DRUG LABEL
Date: 20200520

ACTIVE INGREDIENTS: ALCOHOL 70 mL/100 mL
INACTIVE INGREDIENTS: CITRIC ACID MONOHYDRATE; HYDROXYPROPYL GUAR (2500-4500 MPA.S AT 1%); WATER

PROBALANCE Hand Sanitizer Advanced Gel

PROBALANCE Hand Sanitizer Advanced Gel

Drug Facts

Purpose

Antiseptic

Use

Hand Sanitizer to help reduce bacteria on the skin.

Warnings

Flammable. Keep away from source of heat, fire or flame.

For external use only. Not for Consumption.

When using this product avoid contact with eyes. If contact occurs, rinse thoroughly with water.

Stop use and ask a doctor if irritation or redness develops and lasts.

Keep out of reach of children. If swallowed, get medical help or contact a Poison Control Center right away.

Directions

- place enough product in your palm to thoroughly cover your hands and rub hands together until dry.
- children under 6 years should be supervised when using this product.

Inactive ingredients

Water, hydroxypropyl guar, citric acid

Active ingredient

Alcohol 70% v/v

Other information

- store at a temperature below 110 F (43 C).
- may discolor certain fabrics or surfaces.

Package Label - Principal Display Panel

78072-501-10 - 1 gallon